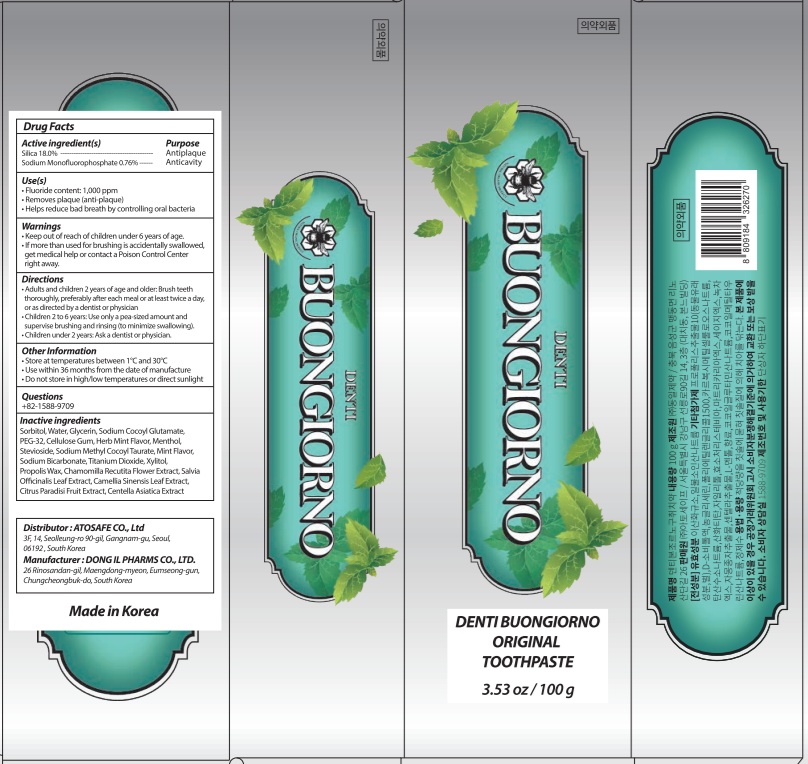 DRUG LABEL: DENTI BUONGIORNO ORIGINAL TOOTH
NDC: 73242-1120 | Form: PASTE, DENTIFRICE
Manufacturer: DONG IL PHARMS CO.,LTD
Category: otc | Type: HUMAN OTC DRUG LABEL
Date: 20251014

ACTIVE INGREDIENTS: SILICON DIOXIDE 18 g/100 g; SODIUM MONOFLUOROPHOSPHATE 0.76 g/100 g
INACTIVE INGREDIENTS: SORBITOL; WATER; GLYCERIN; SODIUM COCOYL GLUTAMATE

Active ingredient(s)

Silica 18.0%

Sodium Monofluorophosphate 0.76%

Purpose

Antiplaque, Anticavity

Warnings

• Keep out of reach of children under 6 years of age.
• If more than used for brushing is accidentally swallowed, get medical help or contact a Poison Control Center right away.

KEEP OUT OF REACH OF CHILDREN

Keep out of reach of childrenunder 6 years of age.

INDICATIONS AND USAGE

Use(s)

• Fluoride content: 1,000 ppm

• Removes plaque (anti-plaque)
• Helps reduce bad breath by controlling oral bacteria

Directions

• Adults and children 2 years of age and older: Brush teeth thoroughly, preferably after each meal or at least twice a day, or as directed by a dentist or physician
• Children 2 to 6 years: Use only a pea-sized amount and supervise brushing and rinsing (to minimize swallowing).
• Children under 2 years: Ask a dentist or physician.

Other Information

• Store at temperatures between 1°C and 30°C
• Use within 36 months from the date of manufacture
• Do not store in high/low temperatures or direct sunlight

Questions

+82-1588-9709

Inactive ingredients

Sorbitol, Water, Glycerin, Sodium Cocoyl Glutamate, PEG-32, Cellulose Gum, Herb Mint Flavor, Menthol, Stevioside, Sodium Methyl Cocoyl Taurate, Mint Flavor, Sodium Bicarbonate, Titanium Dioxide, Xylitol, Propolis Wax, Chamomilla Recutita Flower Extract, Salvia Officinalis Leaf Extract, Camellia Sinensis Leaf Extract, Citrus Paradisi Fruit Extract, Centella Asiatica Extract